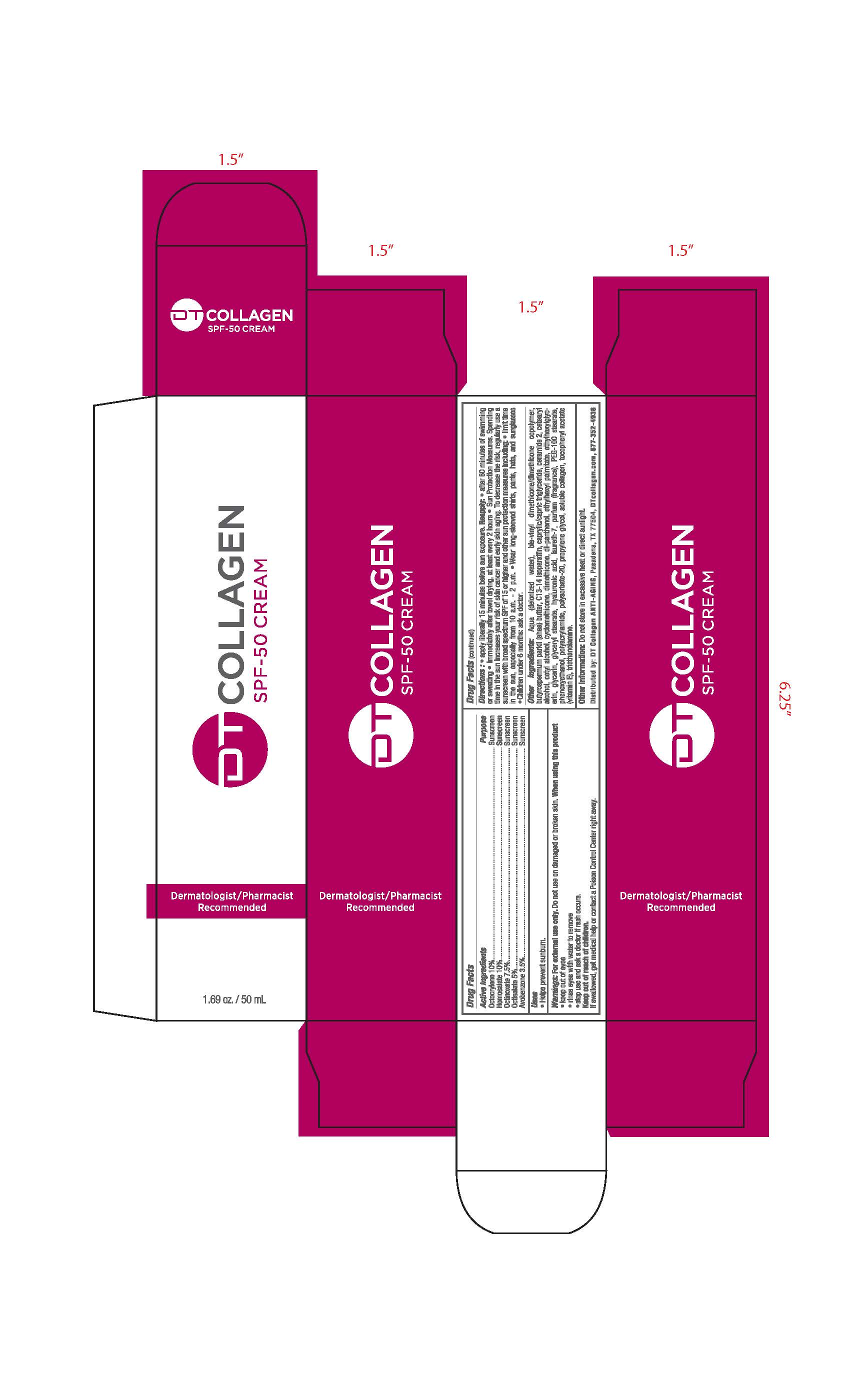 DRUG LABEL: DT Collagen
NDC: 70522-001 | Form: CREAM
Manufacturer: DT Collagen, Inc.
Category: otc | Type: HUMAN OTC DRUG LABEL
Date: 20171215

ACTIVE INGREDIENTS: HOMOSALATE 10 mg/1 mL; OCTOCRYLENE 10 mg/1 mL; OCTINOXATE 7.5 mg/1 mL; OCTISALATE 5 mg/1 mL; AVOBENZONE 3.5 mg/1 mL
INACTIVE INGREDIENTS: WATER; SHEA BUTTER; C13-14 ISOPARAFFIN; CETOSTEARYL ALCOHOL; CETYL ALCOHOL; DIMETHICONE 100; PANTHENOL; ETHYLHEXYL PALMITATE; ETHYLHEXYLGLYCERIN; GLYCERIN; GLYCERYL STEARATE SE; HYALURONIC ACID; LAURETH-7; PEG-100 STEARATE; PHENOXYETHANOL; POLYACRYLAMIDE (10000 MW); POLYSORBATE 20; COLLAGEN, SOLUBLE, FISH SKIN; .ALPHA.-TOCOPHEROL ACETATE; .ALPHA.-TOCOTRIENOL; TRIETHANOLAMINE OLEATE; CAPRYLIC/CAPRIC/LINOLEIC TRIGLYCERIDE; CERAMIDE 2; CYCLOMETHICONE; PROPYLENE GLYCOL 2-OLEATE

DT Collagen

ACTIVE INGREDIENT

Octocrylane 10%, Homosalate 10%, Octinoxate 7.5%, Octinoxate 5%, Avobenzone 3.5%

PURPOSE

Sunscreen

INDICATIONS AND USAGE

Helps prevent sunburn

WARNINGS

For external use only.

Do not use on damaged or borken skin.

When using this product: keep out of eyes, rinse eyes with water to remove, stop use and ask a doctor if rash occurs.

If swallowed, get medical help or contact a Poison Control Center right away.

Keep out of reach of children.

Directions

Apply liberally 15 minutes before sun exposure.

Reapply: after 80 minutes of swimming or sweating, immediatly after towel drying, at least every 2 hours.

Children under 6 months ask a doctor.

Other information

Do not store in excessive heat or direct sunlight.

INACTIVE INGREDIENT

Aqua, vinyl dimethicone copolymer, shea butter, C13-14 isoparafin, caprylic/capric triglyceride, ceramide2, cetearyl alcohol, cetyl alcohol, cyclomethicone, dimethicone, di=panthenol, ethylhexyl palimitate, ethylhexylglycerin, glycerin, glyceryl stearate, hyaluronic acid, laureth-7, PEG-100, stearate, phenoxyethanol, polyacrylamide, polosorbate 20, propyleneylycol, soluble collagen, tocopheryl acetate, triethanolamine